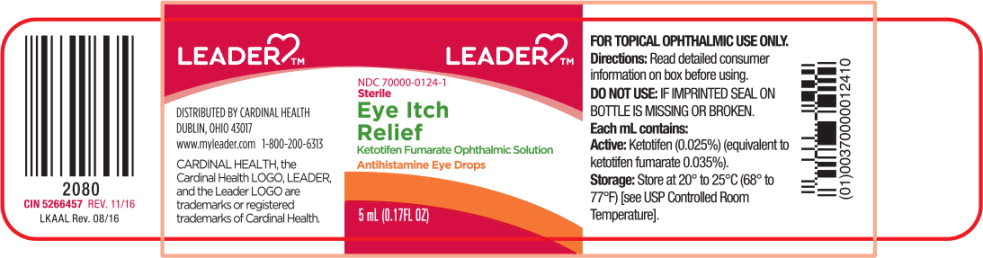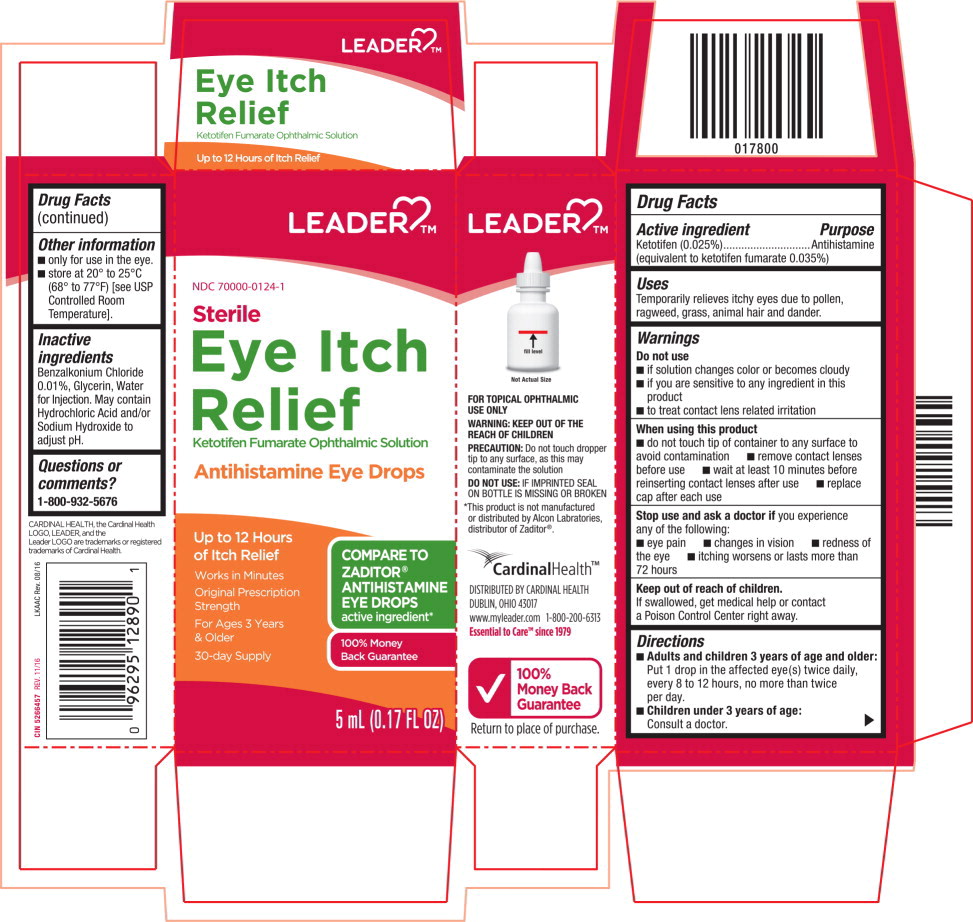 DRUG LABEL: Eye Itch Relief
NDC: 70000-0124 | Form: SOLUTION/ DROPS
Manufacturer: CARDINAL HEALTH 110, LLC. DBA LEADER
Category: otc | Type: HUMAN OTC DRUG LABEL
Date: 20250912

ACTIVE INGREDIENTS: KETOTIFEN FUMARATE 0.35 mg/1 mL
INACTIVE INGREDIENTS: BENZALKONIUM CHLORIDE; GLYCERIN; WATER

Drug Facts

Active Ingredient

Ketotifen (0.025%) (equivalent to ketotifen fumarate 0.035%)

Purpose

Antihistamine

Uses

Temporarily relieves itchy eyes due to pollen, ragweed, grass, animal hair and dander.

Warnings

Do not use

- if solution changes color or becomes cloudy
- if you are sensitive to any ingredient in this product
- to treat contact lens related irritation

When using this product

- do not touch the tip of container to any surface to avoid contamination
- remove contact lenses before use
- wait at least 10 minutes before reinserting contact lens after use
- replace cap after each use

Stop use and ask a doctor if you experience any of the following:

- eye pain
- changes in vision
- redness of the eye
- itching worsens or lasts more than 72 hours

Keep out of reach of children

If swallowed, get medical help or contact a Poison Control Center right away.

Directions

- Adults and children 3 years of age and older: Put 1 drop in the affected eye(s) twice daily, every 8 to 12 hours, no more than twice per day.
- Children under 3 years of age: Consult a doctor

Other information

- only for use in the eye.
- store at 20° to 25°C (68° to 77°F) [see USP Controlled Room Temperature].

Inactive ingredients

Benzalkonium Chloride 0.01%, Glycerin, Water for Injection. May contain Hydrochloric Acid and/or Sodium Hydroxide to adjust pH.

Questions or comments?

1-800-932-5676

.

*This product is not manufactured or distributed by Alcon Laboratories, distributor of Zaditor®.

CardinalHealth™

DISTRIBUTED BY CARDINAL HEALTH

DUBLIN, OHIO 43017

www.myleader.com 1-800-200-6313

Essential to Care™ since 1979

100% Money Back Guarantee

Return to place of purchase.

2080 | CIN 5266457 REV. 11/16 | LKAAL Rev. 08/16
 | CIN 5266457 REV. 11/16 | LKAAC Rev. 08/16

Principal Display Panel Text for Container Label:

LEADER™

NDC 70000-0124-1

Sterile

Eye Itch

Relief

Ketotifen Fumarate Ophthalmic Solution

Antihistamine Eye Drops

5 mL (0.17FL OZ)

Principal Display Panel Text for Carton Label:

LEADER™

NDC 70000-0124-1

Sterile

Eye Itch

Relief

Ketotifen Fumarate Ophthalmic Solution

Antihistamine Eye Drops

Up to 12 Hours

of Itch Relief

Works in Minutes

Original Prescription Strength

For Ages 3 Years & Older

30-day Supply

COMPARE TO ZADITOR® ANTIHISTAMINE EYE DROPS Active ingredient*

100% Money Back Guarantee

5 mL (0.17 FL OZ)